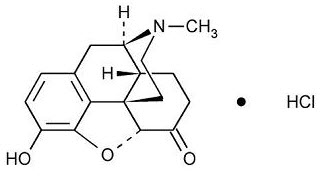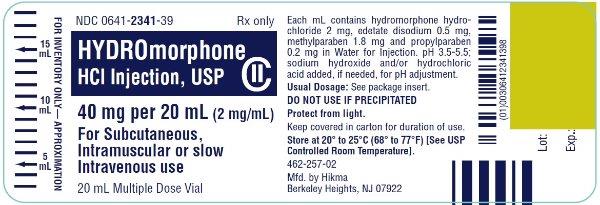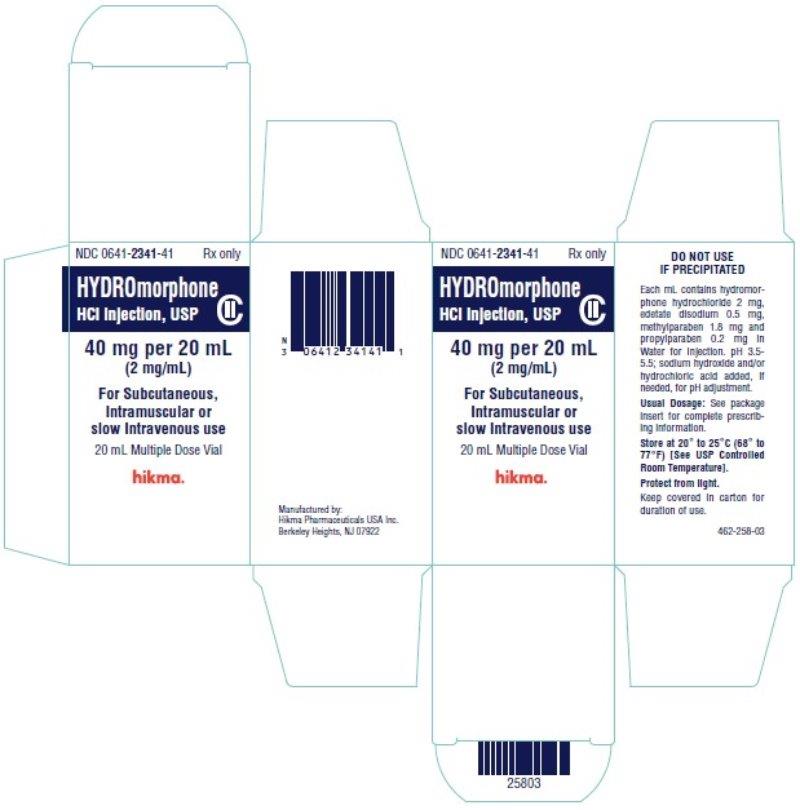 DRUG LABEL: Hydromorphone Hydrochloride
NDC: 0641-0121 | Form: INJECTION
Manufacturer: Hikma Pharmaceuticals USA Inc.
Category: prescription | Type: HUMAN PRESCRIPTION DRUG LABEL
Date: 20260302
DEA Schedule: CII

ACTIVE INGREDIENTS: HYDROMORPHONE HYDROCHLORIDE 2 mg/1 mL
INACTIVE INGREDIENTS: EDETATE DISODIUM 0.5 mg/1 mL; METHYLPARABEN 1.8 mg/1 mL; PROPYLPARABEN 0.2 mg/1 mL; WATER; SODIUM HYDROXIDE; HYDROCHLORIC ACID

HYDROMORPHONE HYDROCHLORIDE INJECTION, USP
CII
Rx only

DESCRIPTION

Hydromorphone Hydrochloride Injection, USP is a sterile solution intended for subcutaneous, intramuscular or slow intravenous injection. Each mL contains hydromorphone hydrochloride 2 mg, edetate disodium 0.5 mg, methylparaben 1.8 mg and propylparaben 0.2 mg in Water for Injection. The pH range is 3.5-5.5; sodium hydroxide and/or hydrochloric acid added, if needed, for pH adjustment. Hydromorphone is a semisynthetic phenanthrene alkaloid of opium; it is classified pharmacologically as a narcotic analgesic. Hydromorphone hydrochloride may be named chemically as 4,5α-Epoxy-3-hydroxy-17-methylmorphinan-6-one hydrochloride, with the following structural formula:

C17H19NO3• HCl M.W. 321.80

Hydromorphone hydrochloride occurs as a fine, white or practically white, crystalline powder and is freely soluble in water and sparingly soluble in alcohol.

CLINICAL PHARMACOLOGY

Hydromorphone resembles morphine both structurally and pharmacologically. Like other narcotic analgesics, hydromorphone exerts its principal pharmacological effects on the central nervous system and gastrointestinal tract. Its primary action of therapeutic value is analgesia. The analgesic effects of hydromorphone are due to its central action; however, the precise mechanism of action of hydromorphone and other opiates is not known, although it is believed to relate to the existence of opiate receptors in the central nervous system. Hydromorphone, like other narcotic analgesics, appears to increase the patient’s tolerance for pain and to decrease the perception of suffering, although the presence of the pain itself may still be recognized.

In addition to analgesia, narcotics commonly produce such CNS effects as drowsiness, alterations in mood and mental clouding. Hydromorphone is reported to produce analgesia with less sedation than morphine. This may be an advantage in the postoperative period, since the patient with a less-clouded sensorium is better able to cooperate in early ambulation procedures. Likewise, cancer patients can be relieved of pain yet remain sufficiently alert to function within the scope of their underlying physical disorder. Narcotic analgesics also depress various respiratory centers, depress the cough reflex, constrict the pupils, elevate cerebrospinal fluid pressure, produce transient hyperglycemia and enhance parasympathetic activity.

Narcotic analgesics may cause nausea and vomiting by stimulating the chemoreceptor trigger zone (CTZ); however, they also depress the vomiting center, so that subsequent doses are unlikely to produce vomiting. Nausea and vomiting are significantly more common in ambulatory than in recumbent patients. Narcotic analgesics, including hydromorphone, increase the tone and decrease the propulsive contractions of the smooth muscle of the gastrointestinal tract. The resultant prolongation in gastrointestinal transit time is responsible for hydromorphone’s constipating effect. Because narcotics may increase biliary tract pressure, some patients with biliary colic may experience worsening rather than relief of pain.

While narcotics generally increase the tone of urinary tract smooth muscle, the net effect tends to be variable, in some cases producing urinary urgency, in others, difficulty in urination. Narcotics have also been reported to cause antidiuretic hormone (ADH) to be released, thereby reducing urine output.

In therapeutic dosage, opiates do not usually exert major effects on the cardiovascular system. However, some patients exhibit a propensity to develop orthostatic hypotension and fainting. Rapid intravenous injection is more likely to precipitate a fall in blood pressure than are intramuscular or subcutaneous injections.

Narcotic analgesics cause histamine release, which appears to be responsible for wheals or urticaria sometimes seen at the site of injection. Histamine release may also produce dilation of cutaneous blood vessels, with resultant flushing of the face and neck, pruritus and sweating.

Hydromorphone is well absorbed after parenteral administration.

After intramuscular administration, hydromorphone has a slightly more rapid onset and slightly shorter duration of analgesia than morphine. The major pathway of hydromorphone metabolism is conjugation with glucuronic acid in the liver; hydromorphone glucuronide is excreted primarily in the urine.

INDICATIONS AND USAGE

Hydromorphone Hydrochloride Injection is indicated for the relief of moderate to severe pain such as that due to: surgery, cancer, trauma (soft tissue and bone), biliary colic, myocardial infarction, burns, renal colic.

CONTRAINDICATIONS

Hydromorphone Hydrochloride Injection is contraindicated in patients with a known hypersensitivity to hydromorphone, in the presence of an intracranial lesion associated with increased intracranial pressure and whenever ventilatory function is depressed (chronic obstructive pulmonary disease, cor pulmonale, emphysema, kyphoscoliosis, status asthmaticus). [See WARNINGS.]

Narcotic analgesics, including hydromorphone, are contraindicated in premature infants or during labor when delivery of a premature infant is anticipated.

WARNINGS

RESPIRATORY DEPRESSION

Hydromorphone produces dose-related respiratory depression by acting directly on brain stem respiratory centers. Hydromorphone also affects centers that control respiratory rhythm and may produce irregular and periodic breathing.

HEAD INJURY AND INCREASED INTRACRANIAL PRESSURE

The respiratory depressant effects of hydromorphone and its capacity to elevate cerebrospinal fluid pressure may be markedly exaggerated in the presence of head injury, other intracranial lesions or a pre-existing increase in intracranial pressure.

Furthermore, hydromorphone produces adverse reactions which may obscure the clinical course of patients with head injuries. In such patients, hydromorphone must be used with extreme caution and only if its use is deemed essential.

ACUTE ABDOMINAL CONDITIONS

The administration of hydromorphone may obscure the diagnosis or clinical course of patients with acute abdominal conditions.

ASTHMA AND OTHER RESPIRATORY CONDITIONS

Hydromorphone should be used with extreme caution in patients having an acute asthmatic attack, patients with chronic obstructive pulmonary disease or cor pulmonale, patients having a substantially decreased respiratory reserve and patients with pre-existing respiratory depression, hypoxia or hypercapnia. In such patients, even usual therapeutic doses of narcotics may decrease respiratory drive while simultaneously increasing airway resistance to the point of apnea.

INTRAVENOUS USE

If necessary, hydromorphone may be given intravenously, but the injection should be given very slowly (over a period of at least 3 to 5 minutes). Rapid intravenous injection of narcotic analgesics, including hydromorphone, increases the incidence of adverse reactions; severe respiratory depression, apnea, hypotension, peripheral circulatory collapse, cardiac arrest, as well as anaphylactoid reactions, have occurred. Hydromorphone should not be administered intravenously unless a narcotic antagonist and the facilities for resuscitation and assisted or controlled respiration are immediately available. When hydromorphone is given parenterally, especially intravenously, the patient should be lying down.

HYPOTENSIVE EFFECT

The administration of hydromorphone may result in severe hypotension in an individual whose ability to maintain blood pressure has already been compromised by a depleted blood volume or concurrent administration of drugs such as the phenothiazines or certain anesthetics.

Hydromorphone may produce orthostatic hypotension in ambulatory patients.

PRECAUTIONS

GENERAL

Narcotic analgesics, including hydromorphone, should be administered with caution and initial dose reduced in patients with acute abdominal conditions, convulsive disorders, significant hepatic or renal impairment, fever, hypothyroidism, Addison’s disease, ulcerative colitis, prostatic hypertrophy, urethral stricture, patients with recent gastrointestinal or urinary tract surgery and in elderly or debilitated patients. As with any narcotic analgesic agent, the possibility of respiratory depression should be kept in mind and the usual precautions observed.

Caution must be used when injecting any opioid subcutaneously or intramuscularly into chilled areas or in patients with hypotension or shock, since impaired perfusion may prevent complete absorption; if repeated injections are administered, an excessive amount may be suddenly absorbed if normal circulation is reestablished.

Hydromorphone suppresses the cough reflex; as with all narcotics, caution should be exercised when hydromorphone is used postoperatively and in patients with pulmonary disease.

INFORMATION FOR PATIENTS

Hydromorphone may impair the mental and/or physical abilities required for the performance of potentially hazardous tasks, such as driving a vehicle or operating machinery. The concomitant use of alcohol or other central nervous system depressants, including sedatives, hypnotics, tranquilizers, phenothiazines and antihistamines may have an additive effect. Hydromorphone, like other narcotic analgesics, may produce orthostatic hypotension in ambulatory patients. Patients should be cautioned accordingly.

DRUG INTERACTIONS

Hydromorphone should be administered cautiously and in reduced dosage to avoid additive effects when other central nervous system depressants including other narcotic analgesics, general anesthetics, phenothiazines, tricyclic antidepressants, sedative-hypnotics or other CNS depressants (including alcohol) are given concomitantly.

Whenever concomitant therapy with MAO inhibitors and narcotic analgesics, including hydromorphone is to be used, an initial small test dose is advisable to allow observation of excessive narcotic effects or MAOI interaction.

DRUG/LABORATORY TEST INTERACTIONS

Because narcotic analgesics may increase biliary tract pressure, with resultant increase in plasma amylase or lipase levels, determination of these enzyme levels may be unreliable for 24 hours after a narcotic analgesic has been given.

CARCINOGENESIS, MUTAGENESIS, IMPAIRMENT OF FERTILITY

Long-term animal studies have not been performed to assess the carcinogenic potential of hydromorphone, nor are there any other animal or human data available concerning carcinogenesis, mutagenesis or impairment of fertility with this drug.

PREGNANCY

Teratogenic Effects - Pregnancy Category C.

Hydromorphone has been shown to be teratogenic in golden hamsters with a minimal effective teratogenic dose of 19 mg/kg, when given in doses 600 times the usual therapeutic dose in humans. There are no adequate and well-controlled studies in pregnant women. Hydromorphone should be used during pregnancy only if the potential benefit justifies the potential risk to the fetus.

Nonteratogenic Effects.

Dependence has been reported in newborns whose mothers took opiates regularly during pregnancy. The withdrawal signs include irritability and excessive crying, tremors, hyperactive reflexes, increased respiratory rate, increased stools, sneezing, yawning, vomiting and fever. Signs usually appear during the first few days of life.

LABOR AND DELIVERY

Hydromorphone crosses the placental barrier. The closer to delivery and the larger the dose used, the greater the possibility of respiratory depression in the newborn. Hydromorphone should be avoided during labor if delivery of a premature infant is anticipated. If the mother has received narcotic analgesics during labor, newborn infants should be observed closely for signs of respiratory depression. Resuscitation may be required (see OVERDOSAGE). The effect of hydromorphone, if any, on the later growth, development and functional maturation of the child is unknown.

Clinical studies have failed to demonstrate any effect of morphine on the uterus itself or on the pattern of contractions during labor. However, therapeutic doses of morphine have been reported to somewhat increase the duration of labor. The mechanism involved, the clinical significance of this observation, if any, or its relevance to other narcotic analgesics, including hydromorphone, are unknown.

NURSING MOTHERS

It is not known whether hydromorphone is excreted in human milk. However, detectable amounts of other narcotic analgesics have been found in human milk. Although these levels are not considered to be clinically significant after usual therapeutic dosage, since there is the potential for serious adverse reactions in nursing infants from hydromorphone, a decision should be made whether to discontinue nursing or discontinue the drug, taking into account the importance of the drug to the mother.

PEDIATRIC USE

Narcotic analgesics, including hydromorphone, should not be used in premature infants (see CONTRAINDICATIONS). Narcotics are reported to cross the immature blood-brain barrier to a greater extent, thereby producing disproportionate respiratory depression.

Safety and effectiveness of hydromorphone in infants and children have not been established and the optimal pediatric dose has not been determined.

ADVERSE REACTIONS

The major hazards of hydromorphone, as with other narcotic analgesics, are respiratory depression and, to a lesser degree, circulatory depression; respiratory arrest, shock and cardiac arrest have occurred, particularly with overdosage or rapid intravenous administration. Anaphylactoid reactions have been reported when phenanthrene alkaloids of opium are administered intravenously.

CENTRAL NERVOUS SYSTEM:

Sedation, drowsiness, mental clouding, headache, tremor, visual disturbances, weakness, agitation, lethargy, impairment of mental and physical performance, uncoordinated muscle movements, anxiety, fear, euphoria, dysphoria, dizziness, psychological dependence and mood changes.

GASTROINTESTINAL SYSTEM:

Nausea and vomiting occur more frequently in ambulatory than in recumbent patients. Hydromorphone may produce constipation, biliary tract spasm and can increase intraluminal pressure which may endanger surgical anastomosis. Patients with chronic ulcerative colitis may experience increased colonic motility; in patients with acute ulcerative colitis, toxic dilatation has been reported with narcotics.

CARDIOVASCULAR SYSTEM:

Circulatory depression, peripheral circulatory collapse and cardiac arrest have occurred after rapid intravenous injection. Orthostatic hypotension and fainting may occur, especially if a patient stands up suddenly after receiving an injection of hydromorphone. Additionally, hydromorphone may cause tachycardia, bradycardia and palpitations.

GENITOURINARY SYSTEM:

Oliguria, ureteral spasm, spasm of vesical sphincters and urinary retention have been reported.

RESPIRATORY DEPRESSION:

Hydromorphone produces dose-related respiratory depression by acting directly on brain stem respiratory centers. Hydromorphone also affects centers that control respiratory rhythm and may produce irregular and periodic breathing. If significant respiratory depression occurs, it may be antagonized by the use of naloxone hydrochloride. In patients who are physically dependent, small doses of naloxone may be sufficient not only to antagonize respiratory depression but also to precipitate withdrawal phenomena. The dose of naloxone should, therefore, be adjusted accordingly in such patients. Since the duration of action of hydromorphone may exceed that of the antagonist, the patient should be kept under continued surveillance; repeated doses of the antagonist may be required to maintain adequate respiration. Apply other supportive measures when indicated.

ALLERGIC:

Allergic reactions to opiates occur infrequently; pruritus, urticaria and other skin rashes are most common. Anaphylactoid reactions have been reported following intravenous administration of opiates.

OTHER:

Opiate-induced histamine release may be responsible for the flushing of the face, sweating and pruritus often seen with these drugs. Wheals and urticaria at the site of injection are probably related to histamine release. Local tissue irritation, pain and induration have been reported following repeated subcutaneous injection.

DRUG ABUSE AND DEPENDENCE

CONTROLLED SUBSTANCE

Hydromorphone Hydrochloride Injection is a Schedule II controlled narcotic substance.

ABUSE

Hydromorphone is known to be subject to abuse. Opiates produce relaxation, indifference to pain and stress, lethargy and euphoria. Patients who receive narcotics regularly for more than a few days may exhibit mild symptoms, which may not be recognized as withdrawal, upon discontinuation of therapy. However, the overwhelming majority of patients who receive opiates for medical reasons do not develop drug-seeking behavior or compulsive drug use. Personality characteristics play a major role in determining which patients are likely to abuse drugs. Hydromorphone must be administered only under close supervision to patients with a history of drug abuse or dependence.

DEPENDENCE

Psychological dependence, physical dependence and tolerance are known to occur with hydromorphone. Therefore, hydromorphone should be prescribed and administered with caution.

The severity of the abstinence syndrome is related to the degree of dependence, the abruptness of withdrawal and the drug used. If the abstinence syndrome is precipitated by administration of a narcotic antagonist, symptoms appear within a few minutes and are maximal within thirty minutes. Administration of a narcotic antagonist as a means of detecting dependence is not usually recommended. Withdrawal symptoms in patients dependent on hydromorphone include yawning; sweating; lacrimation; rhinorrhea; a restless, tossing sleep; dilated pupils; goose flesh; irritability; tremor; nausea; vomiting and diarrhea. Treatment of the abstinence syndrome is primarily symptomatic and supportive, including maintenance of proper fluid and electrolyte balance.

Tolerance, in which increasingly large doses are required in order to produce the same degree of analgesia, is manifested initially by a shortened duration of analgesic effect and subsequently by decreases in the intensity of analgesia. The rate of development of tolerance varies among patients.

OVERDOSAGE

SIGNS AND SYMPTOMS

Serious overdosage with hydromorphone is characterized by respiratory depression (a decrease in respiratory rate and/or tidal volume, Cheyne-Stokes respiration, cyanosis), extreme somnolence progressing to stupor or coma, skeletal muscle flaccidity, cold and clammy skin and sometimes bradycardia and hypotension. The triad of coma, pinpoint pupils and respiratory depression is strongly suggestive of opiate poisoning. In severe overdosage, particularly by the intravenous route, apnea, circulatory collapse, cardiac arrest and death may occur.

It is difficult to determine what constitutes a standard toxic or lethal dose. Infants and children are believed to be relatively more sensitive to opiates on a body-weight basis. Elderly patients are also comparatively intolerant to opiates.

TREATMENT

Primary attention should be given to the reestablishment of adequate respiratory exchange through provision of a patent airway and assisted or controlled ventilation. The narcotic antagonist naloxone hydrochloride is a specific antidote against respiratory depression which may result from overdosage or unusual sensitivity to narcotics, including hydromorphone. Therefore, an appropriate dose of naloxone hydrochloride should be administered, preferably by the intravenous route in conjunction with ventilatory assistance. Since the duration of action of hydromorphone may exceed that of the antagonist, the patient should be kept under continued surveillance; repeated doses of the antagonist may be required to maintain adequate respiration. An antagonist should not be administered in the absence of clinically significant respiratory or cardiovascular depression. Oxygen, intravenous fluids, vasopressors and other supportive measures should be employed as indicated.

The patient should be closely observed for a rise in temperature or pulmonary complications that may signal the need for institution of antibiotic therapy.

NOTE: In an individual physically dependent on narcotics, the administration of the usual dose of a narcotic antagonist will depend on the degree of physical dependence and the dose of antagonist administered. The use of narcotic antagonists in such individuals should be avoided if possible. If a narcotic antagonist must be used to treat serious respiratory depression in the physically dependent patient, the antagonist should be administered with extreme care and only one-tenth to one-fifth the usual initial dose administered.

DOSAGE AND ADMINISTRATION

The usual starting dose is 1-2 mg subcutaneously orintramuscularly every 4 to 6 hours as necessary for pain control. The dose should be adjusted according to severity of pain, as well as the patient’s underlying disease, age and size. Severe pain can usually be controlled by 3-4 mg every 4 to 6 hours as required. Patients with terminal cancer may become tolerant to narcotic analgesics and may, therefore, require higher doses for adequate pain relief. Should intravenous administration be necessary, the injection should be given very slowly (over at least 3 to 5 minutes, depending on the dose) [see WARNINGS, INTRAVENOUS USE]. A gradual increase in dosage may be required if analgesia is inadequate, tolerance occurs or if pain severity increases. The first sign of tolerance is usually a reduced duration of effect.

Parenteral drug products should be inspected visually for particulate matter and discoloration prior to administration, whenever solution and container permit.

HOW SUPPLIED

Hydromorphone Hydrochloride Injection, USP is available in the following:

2 mg/mL
20 mL Multiple Dose vials packaged individually (NDC 0641-2341-41)

STORAGE

PROTECT FROM LIGHT: Keep covered in carton. Store at 20° to 25°C (68° to 77°F), excursions permitted to 15° to 30°C (59° to 86°F) [See USP Controlled Room Temperature]. Do not use the injection if it is more than slightly discolored or contains a precipitate.

To report SUSPECTED ADVERSE REACTIONS, contact Hikma Pharmaceuticals USA Inc. at 1-877-845-0689, or the FDA at 1-800-FDA-1088 or www.fda.gov/medwatch.

For Product Inquiry call 1-877-845-0689.

Manufactured by:
Hikma Pharmaceuticals USA Inc.
Berkeley Heights, NJ 07922

Revised April 2020

462-259-02

PRINCIPAL DISPLAY PANEL

NDC 0641-2341-39 Rx only
Hydromorphone
HCl Injection, USP CII
40 mg per 20 mL (2 mg/mL)
For Subcutaneous,
Intramuscular or slow
Intravenous use
20 mL Multiple Dose Vial

NDC 0641-2341-41 Rx only
Hydromorphone
HCl Injection, USP CII
40 mg per 20 mL
(2 mg/mL)
For Subcutaneous,
Intramuscular or
slow Intravenous use
20 mL Multiple Dose Vial